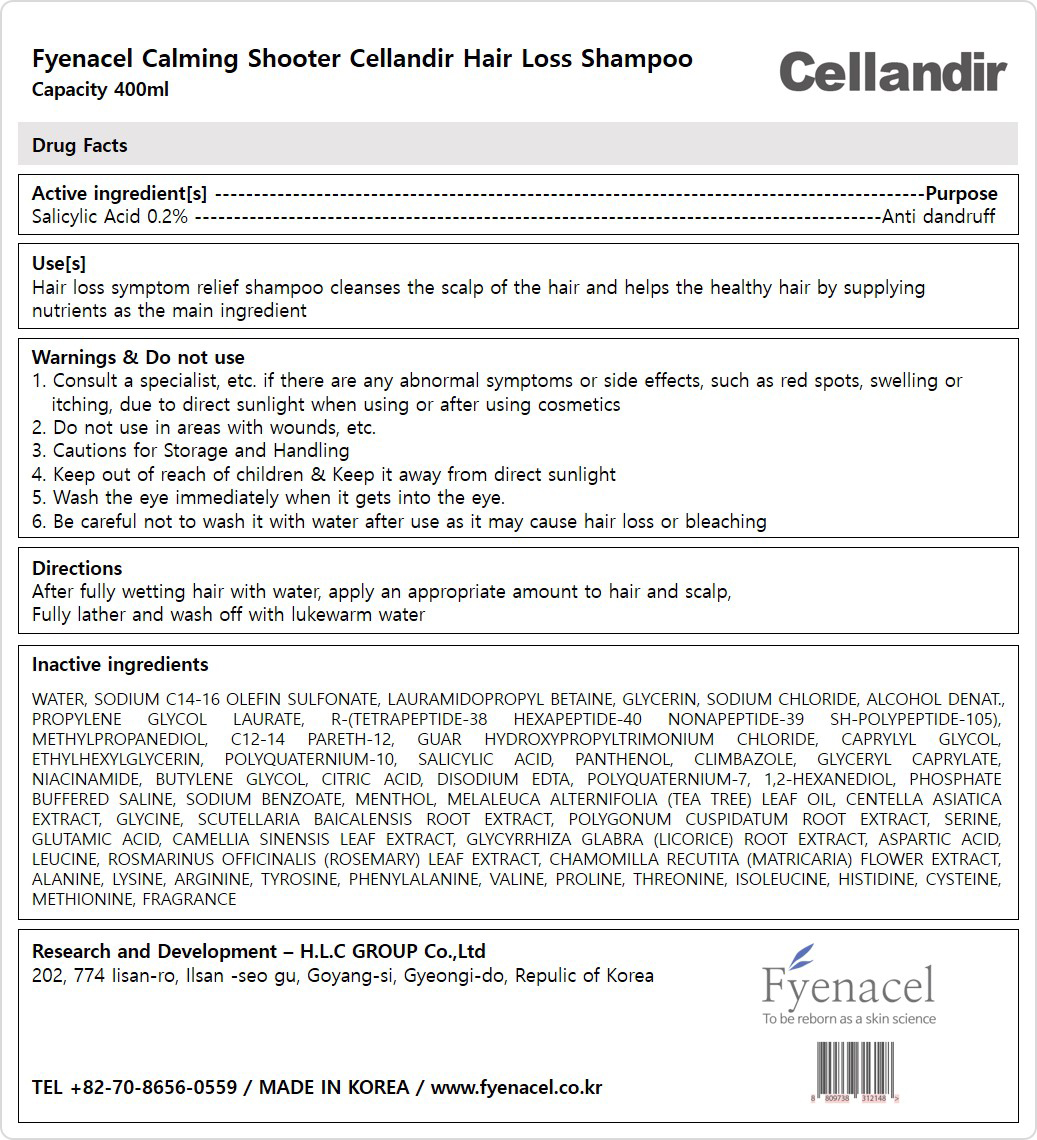 DRUG LABEL: FYENACEL CALMING SHOOTER CELLANDIR HAIR LOSS-Shampoo
NDC: 81555-201 | Form: SHAMPOO
Manufacturer: H.L.C GROUP Co., ltd
Category: otc | Type: HUMAN OTC DRUG LABEL
Date: 20231124

ACTIVE INGREDIENTS: SALICYLIC ACID 2 mg/100 mL
INACTIVE INGREDIENTS: GLYCINE; SCUTELLARIA BAICALENSIS ROOT; SERINE; GLUTAMIC ACID; GREEN TEA LEAF; GLYCYRRHIZA GLABRA; ROSEMARY; CHAMOMILE; LYSINE; ARGININE; PHENYLALANINE; VALINE; METHYLPROPANEDIOL; C12-14 PARETH-12; GUAR HYDROXYPROPYLTRIMONIUM CHLORIDE (1.7 SUBSTITUENTS PER SACCHARIDE); SODIUM CHLORIDE; PROPYLENE GLYCOL MONOLAURATE; BETAINE; NIACINAMIDE; GLYCERYL MONOCAPRYLATE; ALCOHOL; LAURAMIDOPROPYL BETAINE; CAPRYLYL GLYCOL; ETHYLHEXYLGLYCERIN; PANTHENOL; 1,2-HEXANEDIOL; REYNOUTRIA JAPONICA ROOT; ASPARTIC ACID; LEUCINE; ALANINE; TYROSINE; PROLINE; THREONINE; ISOLEUCINE; CYSTEINE; METHIONINE; HISTIDINE; WATER; SODIUM C14-16 OLEFIN SULFONATE; GLYCERIN; CLIMBAZOLE; BUTYLENE GLYCOL; CITRIC ACID MONOHYDRATE; EDETATE DISODIUM ANHYDROUS; POLYQUATERNIUM-7 (70/30 ACRYLAMIDE/DADMAC; 1600000 MW); SODIUM BENZOATE; MENTHOL, UNSPECIFIED FORM; TEA TREE OIL; CENTELLA ASIATICA WHOLE

81555-201 FYENACEL CALMING SHOOTER CELLANDIR SHAMPOO

Active ingredient[s]

SALICYLIC ACID 0.2%

Purpose

Anti dandruff

Use[s]

Hair loss symptom relief shampoo cleanses the scalp of the hair and helps the healthy hair by supplying nutrients as the main ingredient

Warnings

Consult a specialist, etc. if there are any abnormal symptoms or side effects, such as red spots, swelling or itching, due to direct sunlight when using or after using cosmetics

Cautions for Storage and Handling

Wash the eye immediately when it gets into your eye.

Be careful not to wash it with water after use as it may cause hair loss or bleaching

Do not use

in areas with wounds, etc.

Keep out of reach of children & Keep it away from direct sunlight

Directions

After fully wetting hair with water, apply an appropriate amount to hair and scalp,

Fully lather and wash off with lukewarm water

Inactive ingredients

WATER, SODIUM C14-16 OLEFIN SULFONATE, LAURAMIDOPROPYL, BETAINE, GLYCERIN, SODIUM CHLORIDE, ALCOHOL DENAT, PROPYLENE GLYCOL LAURATE, R-(TETRAPEPTIDE-38 HEXAPEPTIDE-40 NONAPEPTIDE-39 SH-POLYPEPTIDE-105), METHYLPROPANEDIOL, C12-14 PARETH-12, GUAR HYDROXYPROPYLTRIMONIUM CHLORIDE, CAPRYLYL GLYCOL, ETHYLHEXYLGLYCERIN, POLYQUATERNIUM-10, PANTHENOL, CLIMBAZOLE, GLYCERYL CAPRYLATE, NIACINAMIDE, BUTYLENE GLYCOL, CITRIC ACID, DISODIUM EDTA, POLYQUATERNIUM-7, 1,2-HEXANEDIOL, PHOSPHATE BUFFERED SALINE, SODIUM BENZOATE, MENTHOL, MELALEUCA ALTERNIFOLIA (TEA TREE) LEAF OIL, CENTELLA ASIATICA EXTRACT, GLYCINE, SCUTELLARIA BAICALENSIS ROOT EXTRACT, POLYGONUM CUSPIDATUM ROOT EXTRACT, SERINE, GLUTAMIC ACID, CAMELLIA SINENSIS LEAF EXTRACT, GLYCYRRHIZA GLABRA (LICORICE) ROOT EXTRACT, ASPARTIC ACID, LEUCINE, ROSMARINUS OFFICINALIS (ROSEMARY) LEAF EXTRACT, CHAMOMILLA RECUTITA (MATRICARIA) FLOWER EXTRACT, ALANINE, LYSINE, ARGININE, TYROSINE, PHENYLALANINE, VALINE, PROLINE, THREONINE, ISOLEUCINE, HISTIDINE, CYSTEINE, METHIONINE, FRAGRANCE